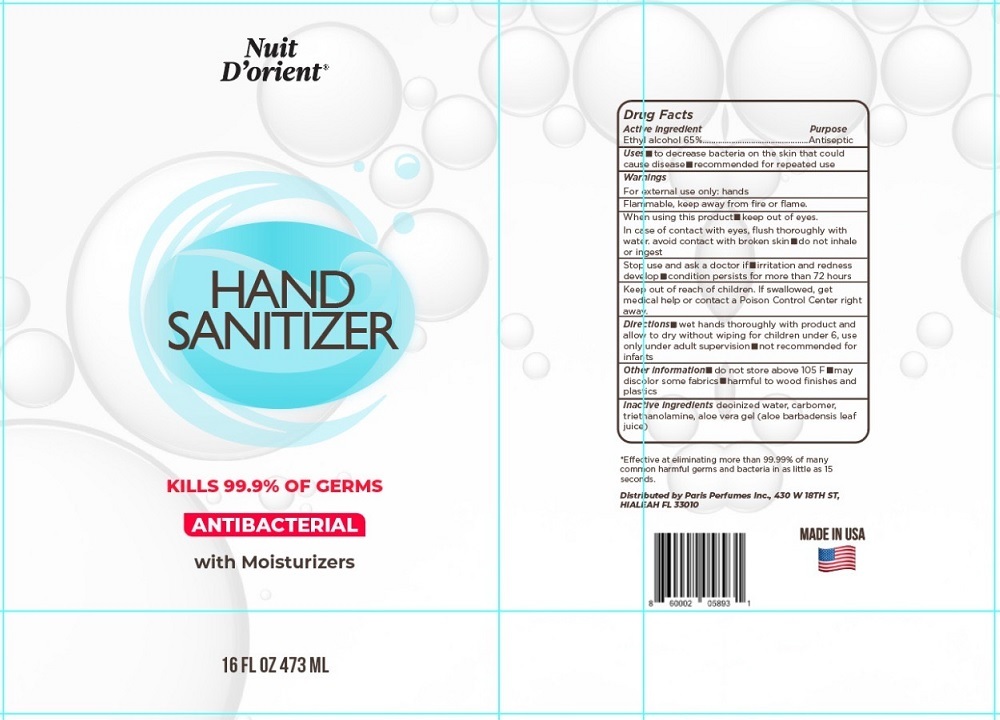 DRUG LABEL: Nuit D Orient HAND SANITIZER
NDC: 79877-065 | Form: GEL
Manufacturer: Paris Perfumes, Inc.
Category: otc | Type: HUMAN OTC DRUG LABEL
Date: 20200729

ACTIVE INGREDIENTS: ALCOHOL 65 mL/100 mL
INACTIVE INGREDIENTS: WATER; CARBOMER HOMOPOLYMER, UNSPECIFIED TYPE; TROLAMINE; ALOE VERA LEAF

Nuit D'orient® HAND SANITIZER

Active ingredient

Ethyl alcohol 65%

Purpose

Antiseptic

Uses

■ to decrease bacteria on the skin that could cause disease ■ recommended for repeated use.

Warnings

For external use only: hands.

Flammable, keep away from fire or flame.

When using this product ■ keep out of eyes. In case of contact with eyes, flush thoroughly with water. avoid contact with broken skin ■ do not inhale or ingest

Stop use and ask a doctor if ■ irritation and redness develop ■ condition persists for more than 72 hours.

Keep out of reach of children. If swallowed, get medical help or contact a Poison Control Center right away.

Directions

■wet hands thoroughly with product and allow to dry without wiping for children under 6, use only under adult supervision ■ not recommended for infants.

Other information

■ do not store above 105 F ■ may discolor some fabrics ■ harmful to wood finishes and plastics.

Inactive Ingredients

deoinized water, carbomer, triethanolamine, aloe vera gel (aloe barbadensis leaf juice)

KILLS 99.9% OF GERMS

ANTIBACTERIAL

with Moisturizers

*Effective at eliminating more than 99.99% of many common harmful germs and bacteria in as little as 15 seconds.

Distributed by Paris Perfumes Inc., 430 W 18TH ST,

HIALEAH FL 33010

MADE IN USA